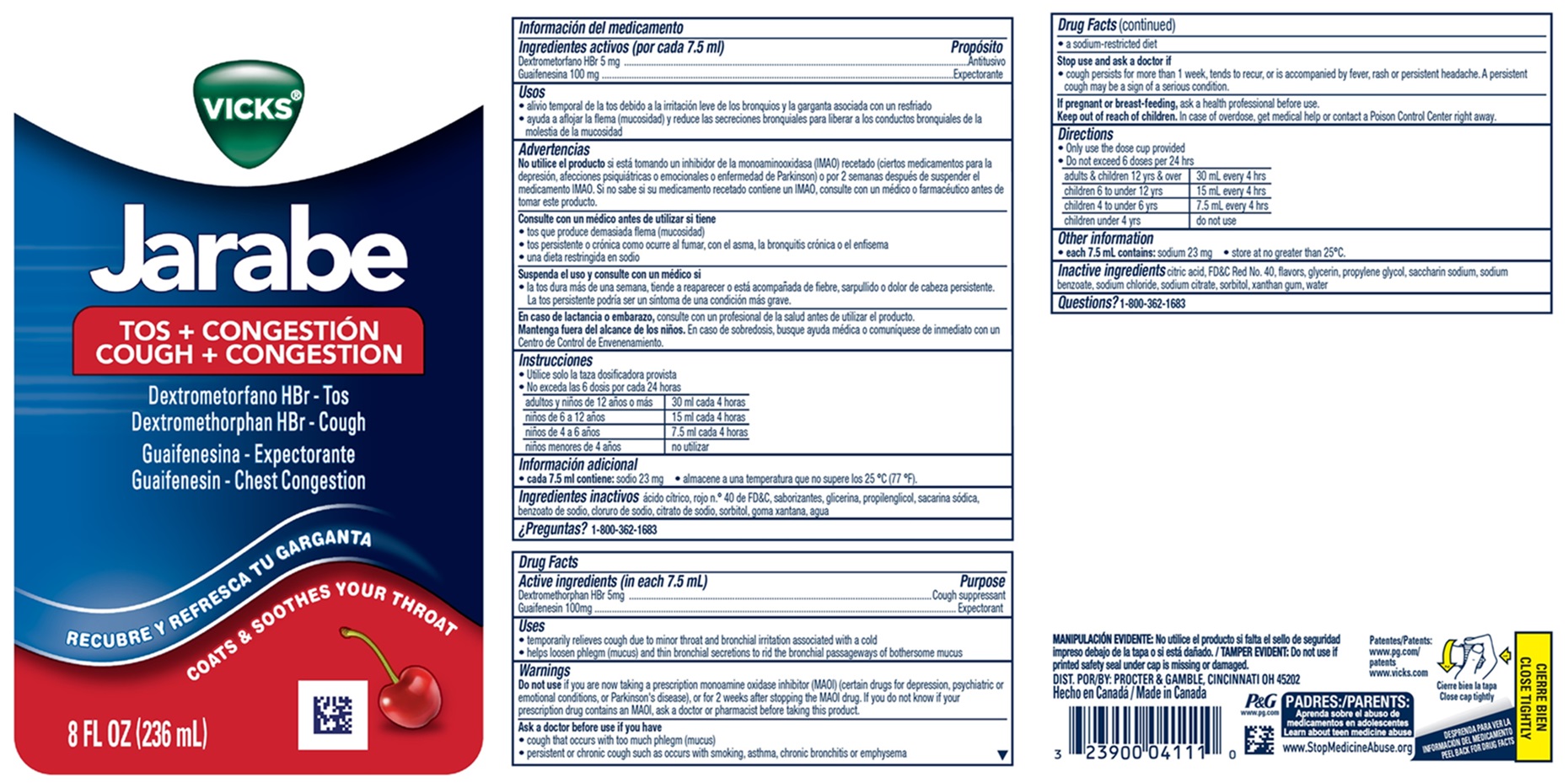 DRUG LABEL: Vicks Jarabe
NDC: 37000-959 | Form: LIQUID
Manufacturer: The Procter & Gamble Manufacturing Company
Category: otc | Type: HUMAN OTC DRUG LABEL
Date: 20251203

ACTIVE INGREDIENTS: DEXTROMETHORPHAN HYDROBROMIDE 5 mg/7.5 mL; GUAIFENESIN 100 mg/7.5 mL
INACTIVE INGREDIENTS: SODIUM CHLORIDE; GLYCERIN; SODIUM BENZOATE; SORBITOL; XANTHAN GUM; ANHYDROUS CITRIC ACID; PROPYLENE GLYCOL; WATER; SACCHARIN SODIUM; SODIUM CITRATE; FD&C RED NO. 40

VICKS®Jarabe Cough + Congestion

Drug Facts

Active ingredients (in each 7.5 mL)

Dextromethorphan HBr 5 mg
Guaifenesin 100 mg

Purpose

Cough suppressant
Expectorant

Uses

- temporarily relieves cough due to minor throat and bronchial irritation associated with a cold
- helps loosen phlegm (mucus) and thin bronchial secretions to rid the bronchial passageways of bothersome mucus

Warnings

Do not use

if you are now taking a prescription monoamine oxidase inhibitor (MAOI) (certain drugs for depression, psychiatric or emotional conditions, or Parkinson's disease), or for 2 weeks after stopping the MAOI drug. If you do not know if your prescription drug contains an MAOI, ask a doctor or pharmacist before taking this product.

Ask a doctor before use if you have

- cough that occurs with too much phlegm (mucus)
- persistent or chronic cough such as occurs with smoking, asthma, chronic bronchitis or emphysema
- a sodium-restricted diet

Stop use and ask a doctor if

cough persists for more than 1 week, tends to recur, or is accompanied by fever, rash or persistent headache. A persistent cough may be a sign of a serious condition.

If pregnant or breast-feeding,

ask a health professional before use.

Keep out of reach of children.

In case of overdose, get medical help or contact a Poison Control Center right away.

Directions

• only use the dose cup provided
• do not exceed 6 doses per 24 hrs

adults & children 12 yrs & over | 30 mL every 4 hrs
children 6 to under 12 yrs | 15 mL every 4 hrs
children 4 to under 6 yrs | 7.5 mL every 4 hrs
children under 4 yrs | do not use

Other information

• each 7.5 mL contains:sodium 23 mg

• store at no greater than 25°C

Inactive ingredients

citric acid, FD&C Red No. 40, flavors, glycerin, propylene glycol, saccharin sodium, sodium benzoate, sodium chloride, sodium citrate, sorbitol, water, xanthan gum

Questions?

1-800-362-1683

TAMPER EVIDENT: Do not use if printed safety seal under cap is missing or damaged

Made in Canada

DIST. BY: PROCTER & GAMBLE, CINCINNATI, OH 45202

PRINCIPAL DISPLAY PANEL - 236 ml Bottle Label

VICKS®

Jarabe

COUGH + CONGESTION

Dextromethorphan HBr - Cough

Guaifensin - Chest Congestion

COATS & SOOTHES YOUR THROAT

8 FL OZ (236 mL)